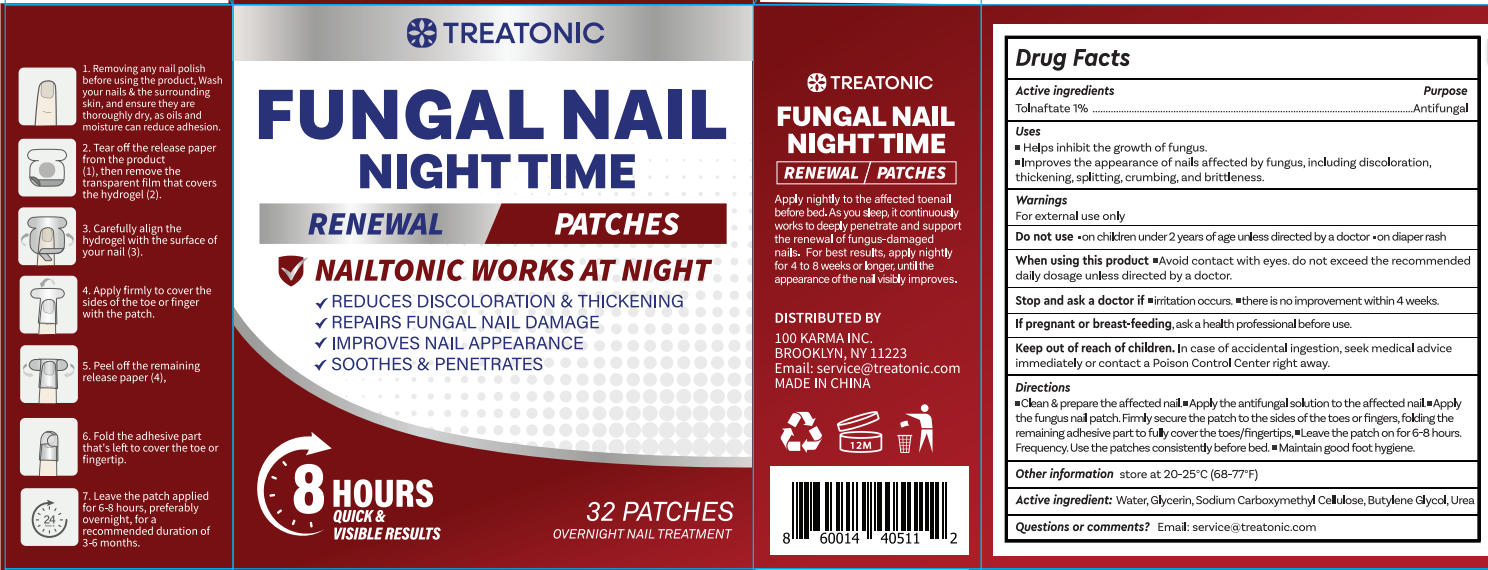 DRUG LABEL: FUNGAL NAIL NIGHTTIME RENEWAL PATCHES
NDC: 85569-009 | Form: PATCH
Manufacturer: 100 KARMA INC
Category: otc | Type: HUMAN OTC DRUG LABEL
Date: 20260301

ACTIVE INGREDIENTS: TOLNAFTATE 1 g/100 1
INACTIVE INGREDIENTS: WATER; GLYCERIN; BUTYLENE GLYCOL; CARBOXYMETHYLCELLULOSE SODIUM; UREA

Update-85569-009-01

ACTIVE INGREDIENT

Tolnaftate 1%

PURPOSE

Antifungal

DOSAGE AND ADMINISTRATION

- Helps inhibit the growth of fungus.
- lmproves the appearance of nails affected by fungus,including discoloration,thickening, splitting, crumbing, and brittleness.

WARNINGS

For external use only

DO NOT USE

on children under 2 years ofage unless directed by a doctor on diaper rash

WHEN USING

Avoid contact with eyes. do not exceed the recommended daly dosage unless directed by a doctor.

ASK DOCTOR

- mirritation occurs.
- there is no improvement within 4 weeks.

PREGNANCY OR BREAST FEEDING

ask a health professional before use.

KEEP OUT OF REACH OF CHILDREN

in case of accidental ingestion, seek medical advice immediately or contact a Poison Control Center right away.

INDICATIONS AND USAGE

▪ Clean & prepare the affected nail.
▪ Apply the antifungal solution to the affected nail.
▪ Apply the fungus nail patch. Firmly secure the patch to the sides of the toes or fingers, folding the remaining adhesive part to fully cover the toes/fingertips.
▪ Leave the patch on for 6–8 hours. Frequency: Use the patches consistently before bed.
▪ Maintain good foot hygiene.

OTHER SAFETY INFORMATION

store at 20-25°C (68-77°F)

INACTIVE INGREDIENT

Water, Glycerin, Sodium Carboxymethy Cellulose, Butylene clycol, Urea

QUESTIONS

Email: service@treatonic.com